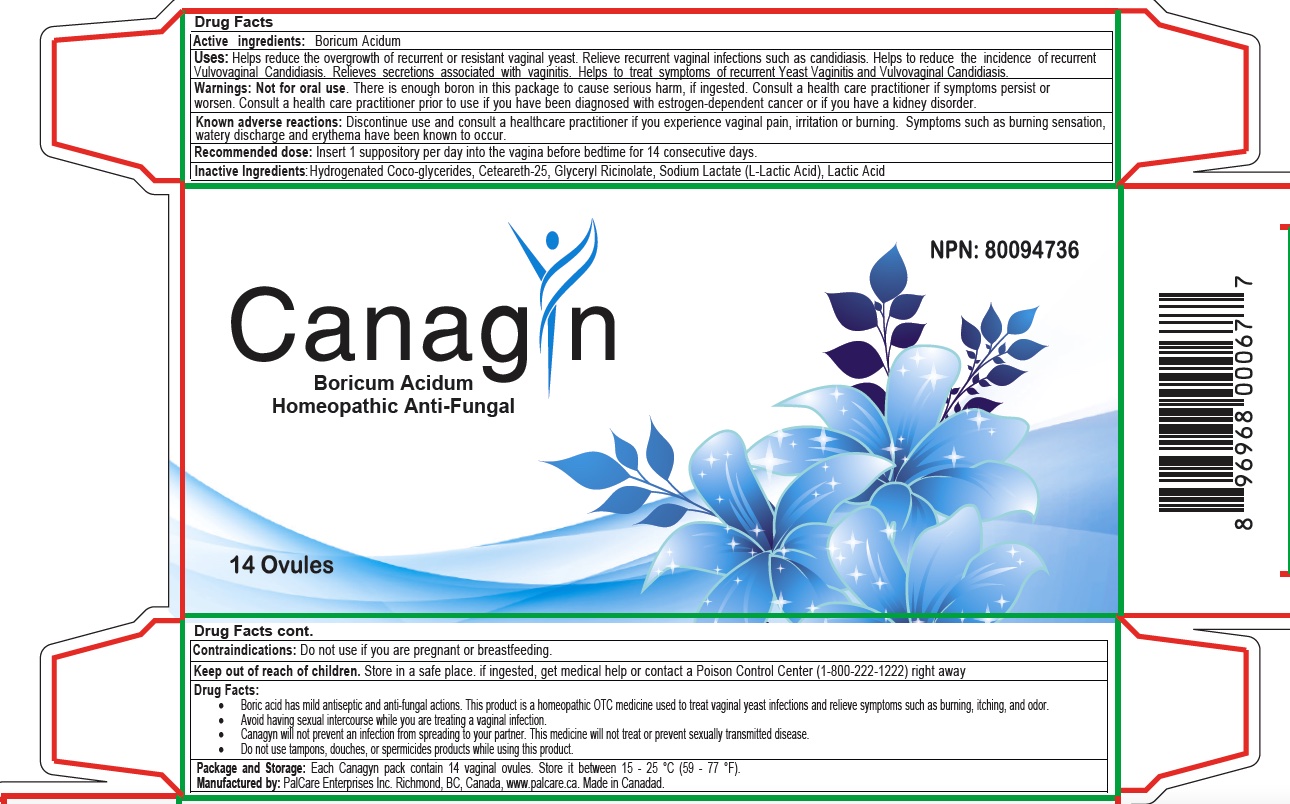 DRUG LABEL: Canagyn
NDC: 82349-120 | Form: SUPPOSITORY
Manufacturer: Palcare Enterprises Inc
Category: homeopathic | Type: HUMAN OTC DRUG LABEL
Date: 20230110

ACTIVE INGREDIENTS: BORIC ACID 0.3 mg/1 1
INACTIVE INGREDIENTS: GLYCERYL RICINOLEATE; CETEARETH-25; LACTIC ACID; HYDROGENATED COCO-GLYCERIDES; SODIUM LACTATE, L-

Homeopathic Antifungal

Active Ingredient(s)

Boricum Acidum

Purpose

Antifungal

Use

Uses: Helps reduce the overgrowth of recurrent or resistant vaginal yeast. Relieve recurrent vaginal infections such as candidiasis. Helps to reduce the incidence of recurrent Vulvovaginal Candidiasis. Relieves secretions associated with vaginitis. Helps to treat symptoms of recurrent Yeast Vaginitis and Vulvovaginal Candidiasis.

Warnings

Not for oral use. There is enough boron in this package to cause serious harm if ingested.

Consult a health care practitioner if symptoms persist or worsen.

Consult a health care practitioner prior to use if you have been diagnosed with estrogen-dependent cancer or if you have a kidney disorder

Do not use if you are pregnant or breastfeeding.

WHEN USING

Consult a health care practitioner if symptoms persist or worsen.

Consult a health care practitioner prior to use if you have been diagnosed with estrogen-dependent cancer or if you have a kidney disorder

STOP USE

Discontinue use and consult a healthcare practitioner if you experience vaginal pain, irritation or burning. Symptoms such as burning sensation, watery discharge, and erythema have been known to occur.

KEEP OUT OF REACH OF CHILDREN

Store in a safe place. if ingested, get medical help or contact a Poison Control Center (1-800-222-1222) right away

Directions

Insert 1 suppository per day into the vagina before bedtime for 14 consecutive days.

Other information

- Boric acid has mild antiseptic and anti-fungal actions. This product is a homeopathic OTC medicine used to treat vaginal yeast infections and relieve symptoms such as burning, itching, and odor.
- Avoid having sexual intercourse while you are treating a vaginal infection.

Canagyn will not prevent an infection from spreading to your partner. This medicine will not treat or prevent sexually transmitted diseases.

- Do not use tampons, douches, or spermicides products while using this product.
- Store it between 15 - 25 °C (59 - 77 °F).

Inactive ingredients

Hydrogenated Coco-glycerides, Ceteareth-25, Glyceryl Ricinolate, Sodium Lactate (L-Lactic Acid), Lactic
Acid